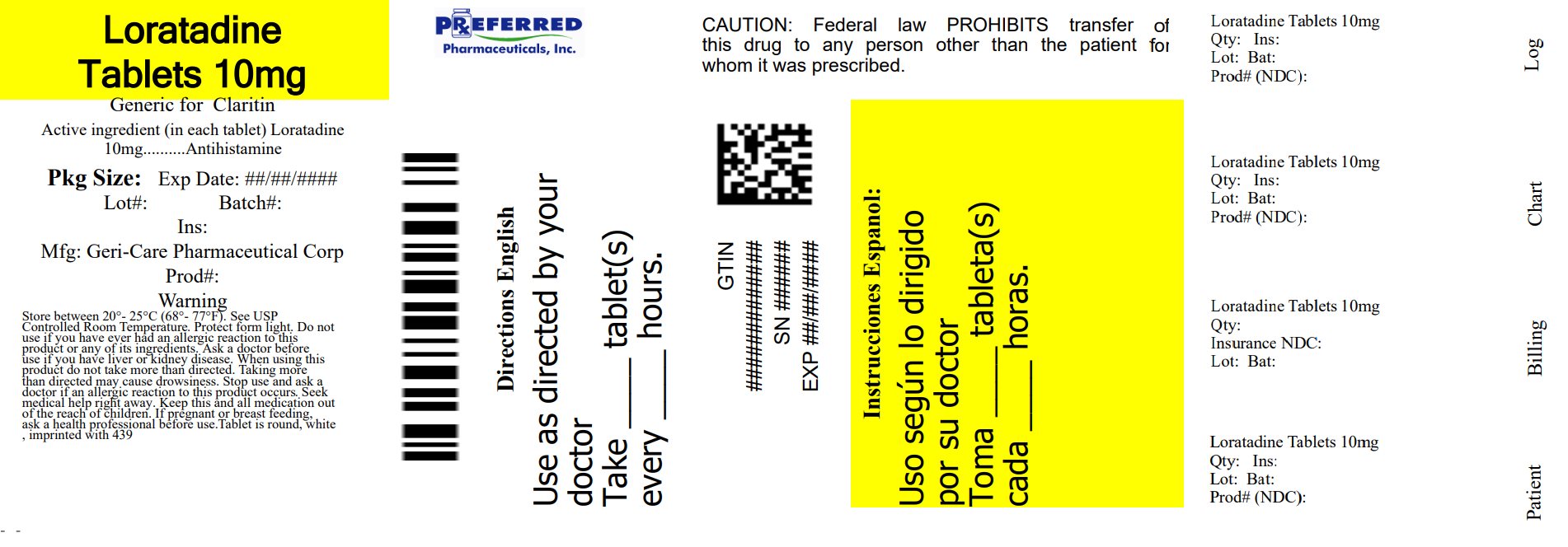 DRUG LABEL: Allergy relief
NDC: 68788-4016 | Form: TABLET
Manufacturer: Preferred Pharmaceuticals Inc.
Category: otc | Type: HUMAN OTC DRUG LABEL
Date: 20250829

ACTIVE INGREDIENTS: LORATADINE 10 mg/1 1
INACTIVE INGREDIENTS: SODIUM STARCH GLYCOLATE TYPE A CORN; LACTOSE MONOHYDRATE; MAGNESIUM STEARATE; MICROCRYSTALLINE CELLULOSE

788S (658)

Active ingredient (in each tablet)

Loratadine, USP 10 mg

Purpose

Antihistamine

Uses

temporarily relieves these symptoms due to hay fever and other upper respiratory allergies:

- runny nose
- sneezing
- itching of the nose and throat
- itchy, watery eyes

Warnings

Do not use if you have ever had an allergic reaction to this

product or any of its ingredients.

Ask a doctor before use if you have liver or kidney disease.

Your doctor should determine if you need a different dose.

When using this product do not take more than directed.

Taking more than directed may cause drowsiness.

Stop use and ask a doctor if an allergic reaction to this

product occurs. Seek medical help right away.

If pregnant or breast-feeding, ask a health professional before use.

Keep out of reach of children. In case of overdose, get medical help or contact a Poison Control Center right away.

Directions

adults and children 12 years and over | 1 tablet daily; not more than 1 tablet in 24 hours
children under 12 years of age | ask a doctor
consumers with liver or kidney disease | ask a doctor

Other information

- store between 20° to 25°C (68° to 77°F)
- protect from light

Inactive ingredients

lactose monohydrate, magnesium stearate, microcrystalline cellulose, sodium starch glycolate

Questions?

call 1-800-540-3765